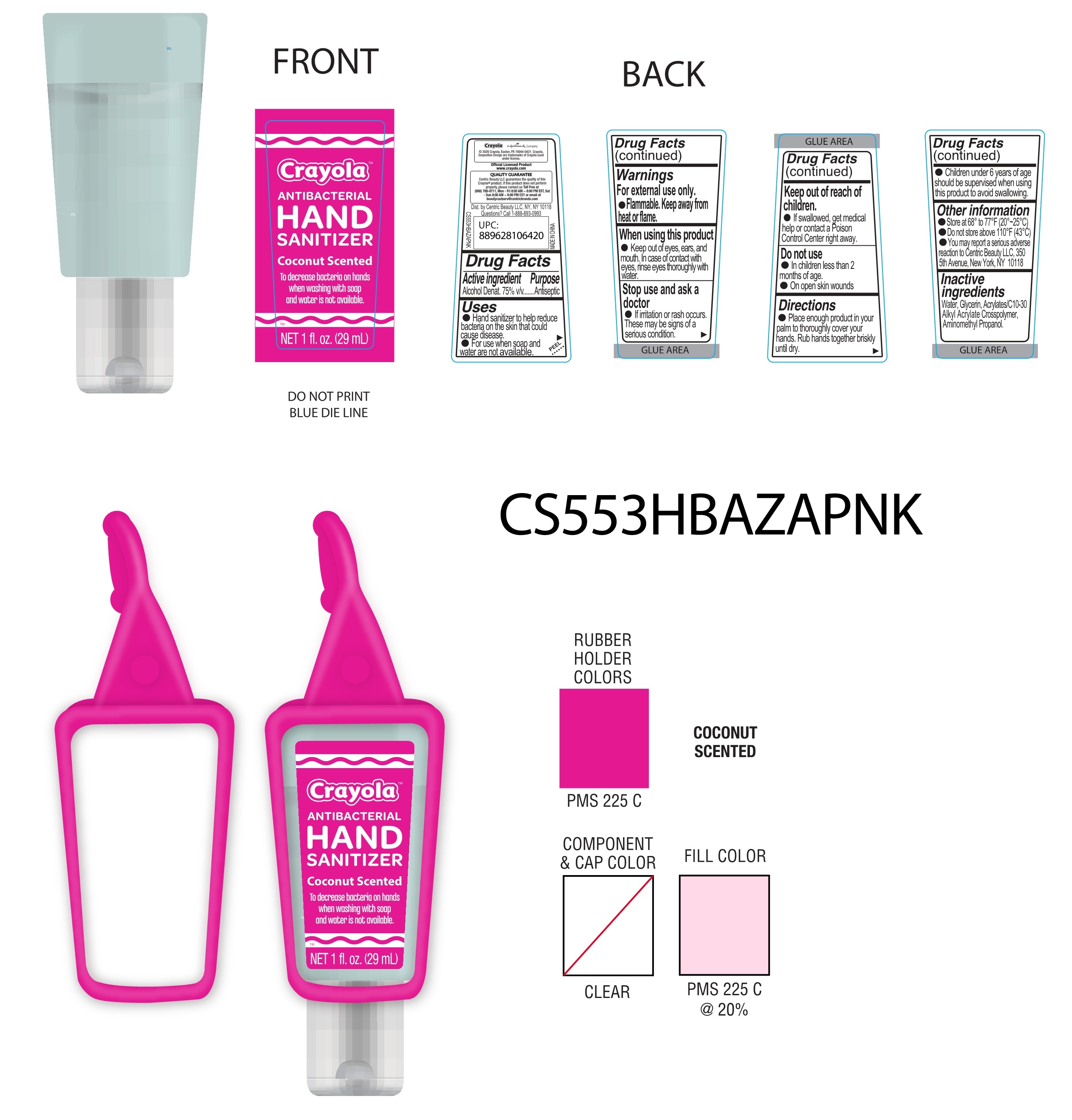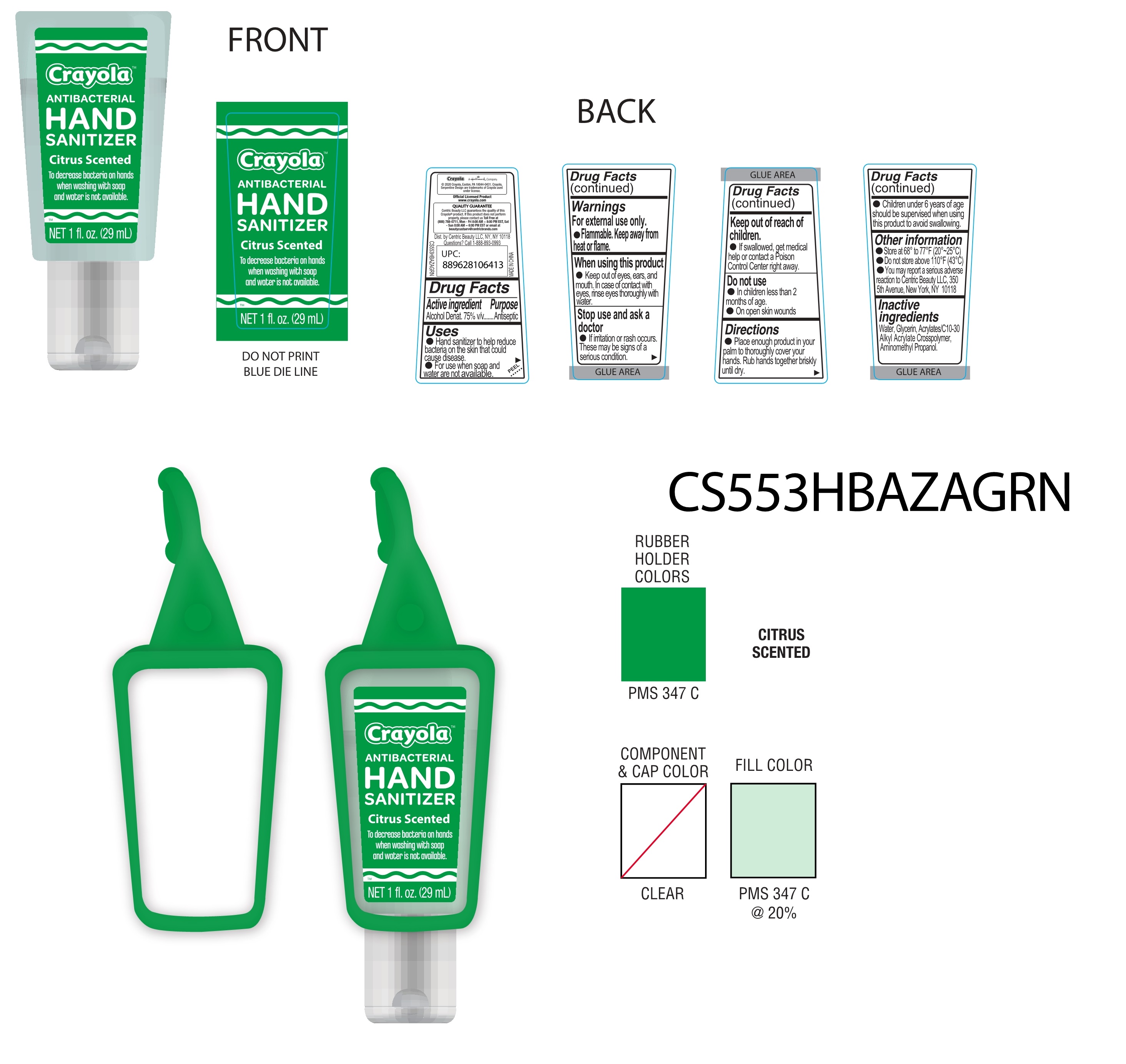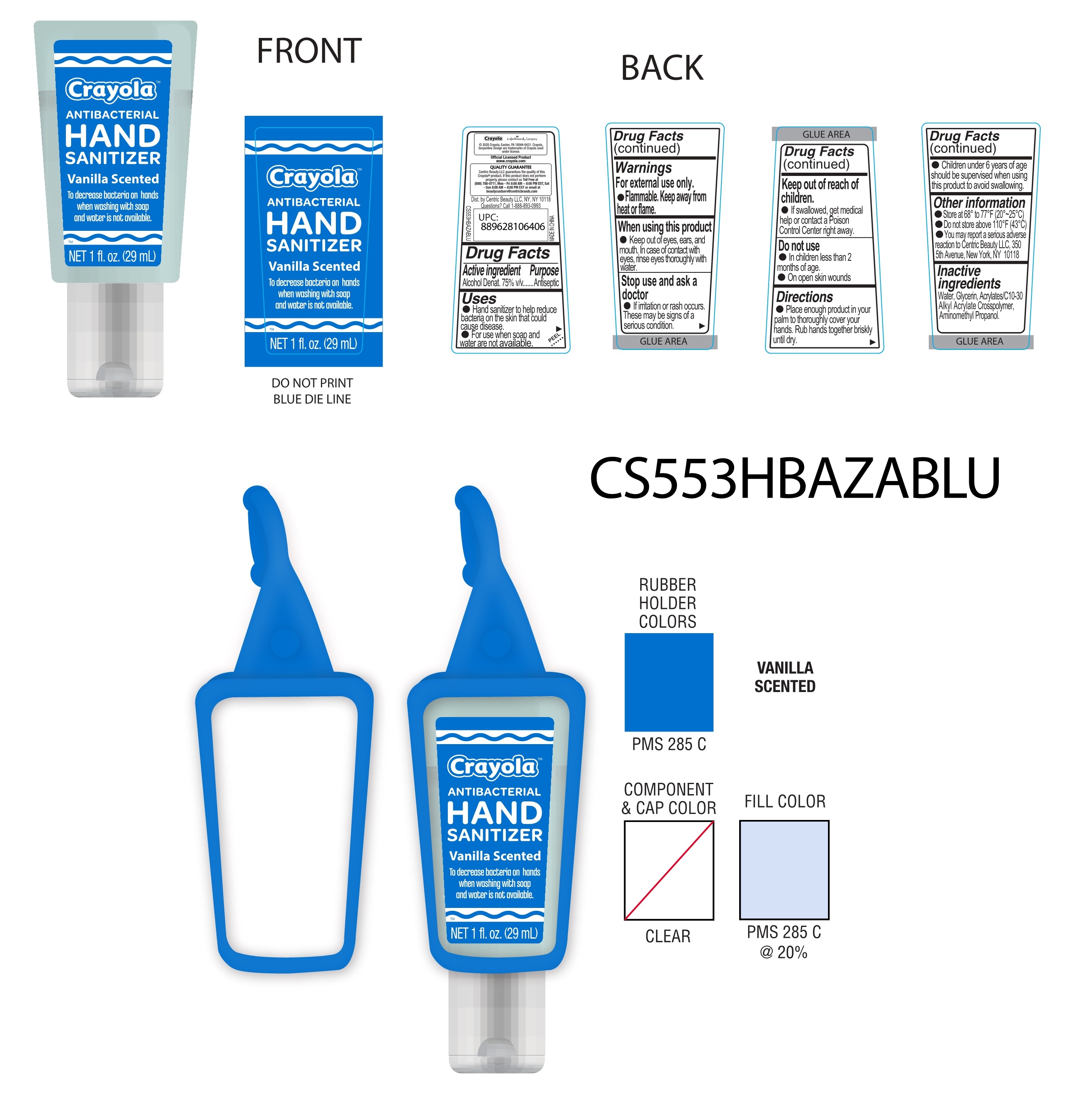 DRUG LABEL: Hand sanitizer
NDC: 81220-001 | Form: GEL
Manufacturer: ZHENG MENG COSMETICS CO.,LTD.
Category: otc | Type: HUMAN OTC DRUG LABEL
Date: 20201210

ACTIVE INGREDIENTS: ALCOHOL 75 mL/100 mL
INACTIVE INGREDIENTS: GLYCERIN; CARBOMER INTERPOLYMER TYPE A (55000 CPS); WATER; AMINOMETHYLPROPANOL

81220-001
Hand sanitizer

Active Ingredient(s)

Alcohol Denat. 75% v/v

Purpose

Antiseptic

Use

Hand sanitizer to help reduce bacteria on the skin that could cause disease.
For use when soaP and water are not availaole.

Warnings

For external use only.
Flammable Keep away from heat or flame.

Do not use

In children less than 2 months of age.
On open skin wounds

When using this product
Keep out of eyes, ears, and mouth. In case of contact with eyes, rinse eyes thorough with water.

Stop use and ask a doctor
If irritation or rash occurs.
These may be signs of a serious condition.

Keep out of reach of children.
If swallowed, get medical help or contact a poison Control Center right away.

Directions

Place enough product in your palm to thorougly cover your hands. Rub hands together briskly until dry.
Children under 6 ears of age should be supervise when using this product to avoid swallowing.

Other information

Store at 68° to 77°F (20°~2 5°C
Do not store above 110°F (43°)
You maY report a serious adverse reaction to Centric BeauTy LLC, 350
5th Avenue, New York, NY 10118

Inactive ingredients

Water, Glycerin, Acrylates/C10-30 Alkyl Acrylate Crosspolymer, Aminomethyl Propanol.